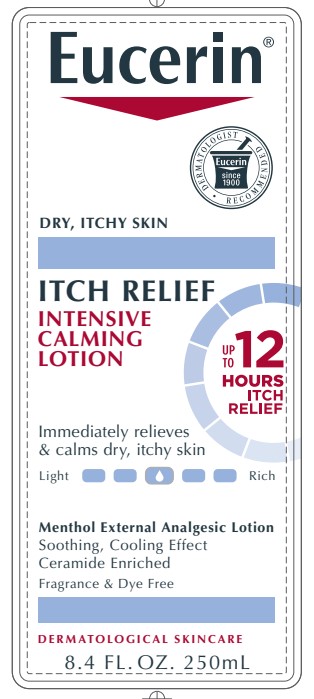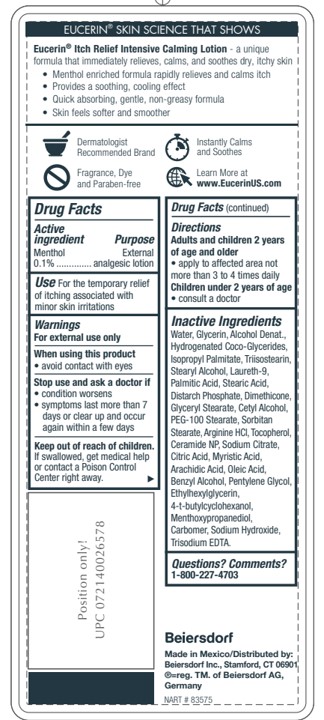 DRUG LABEL: Eucerin Itch Relief Intensive Calming
NDC: 10356-358 | Form: LOTION
Manufacturer: Beiersdorf Inc
Category: otc | Type: HUMAN OTC DRUG LABEL
Date: 20251231

ACTIVE INGREDIENTS: MENTHOL 0.1 g/100 mL
INACTIVE INGREDIENTS: CETYL ALCOHOL; DIMETHICONE; SODIUM CITRATE; BENZYL ALCOHOL; WATER; GLYCERIN; ALCOHOL; PEG-100 STEARATE; GLYCERYL MONOSTEARATE; ETHYLHEXYLGLYCERIN; CARBOMER 980; CITRIC ACID MONOHYDRATE; SORBITAN MONOSTEARATE; ARGININE HYDROCHLORIDE; PENTYLENE GLYCOL; 4-TERT-BUTYLCYCLOHEXANOL; 3-((L-MENTHYL)OXY)PROPANE-1,2-DIOL; SODIUM HYDROXIDE; EDETATE TRISODIUM; TOCOPHEROL; CERAMIDE NP; MYRISTIC ACID; ARACHIDIC ACID; OLEIC ACID; TRIISOSTEARIN; STEARYL ALCOHOL; PALMITIC ACID; STEARIC ACID; HYDROGENATED COCO-GLYCERIDES; ISOPROPYL PALMITATE; POLIDOCANOL

Eucerin Itch Relief Intensive Calming Lotion

ACTIVE INGREDIENT

Menthol 0.1%

PURPOSE

External analgesic lotion

INDICATIONS AND USAGE

Use for the temporary relief of itching associated with minor skin irritations.

WARNINGS

For external use only.

When using this product avoid contact with eyes.

Stop use and ask a doctor if

- condition worsens
- symptoms last more than 7 days or clear up and occur again within a few days
- irritation occurs

Keep out of reach of children. If swallowed, get medical help or contact a Poison Control Center right away.

Questions or comments 1 800 227 4703

INACTIVE INGREDIENT

Ingredients:

Water, Glycerin, Alcohol Denat., Hydrogenated Coco-Glycerides, Isopropyl Palmitate, Triisostearin,
Stearyl Alcohol, Laureth-9, Palmitic Acid, Stearic Acid, Distarch Phosphate, Dimethicone,
Glyceryl Stearate, Cetyl Alcohol, PEG-100 Stearate, Sorbitan Stearate, Arginine HCl, Tocopherol,
Ceramide NP, Sodium Citrate, Citric Acid, Myristic Acid, Arachidic Acid, Oleic Acid,
Benzyl Alcohol, Pentylene Glycol, Ethylhexylglycerin, 4-t-butylcyclohexanol,
Menthoxypropanediol, Carbomer, Sodium Hydroxide, Trisodium EDTA.Inactive Ingredients

Directions

Adults and children 8 years of age and older

- apply to affected area not more than 3 to 4 times daily

Children under 8 years of age

- consult a doctor

PACKAGE LABEL

Eucerin

Itch Relief Intensive Calming Lotion

Dry, Itchy Skin

up to 12 hours itch relief

Immediately relieves and calms dry, itchy skin

Menthol External Analgesic Lotion

Soothing, cooling effect

Ceramide enriched

Fragrance and Dye Free

Dermatological skincare